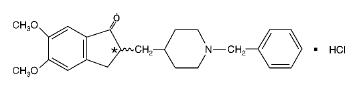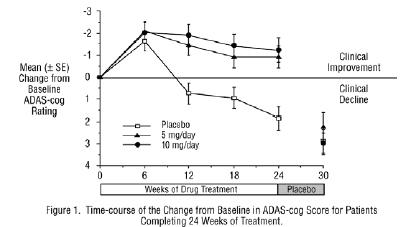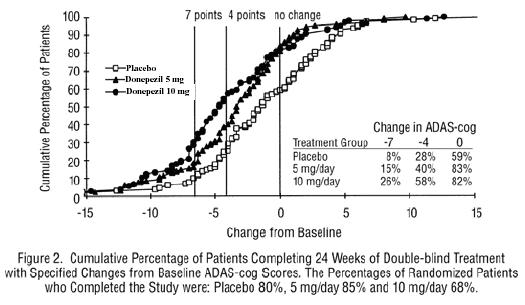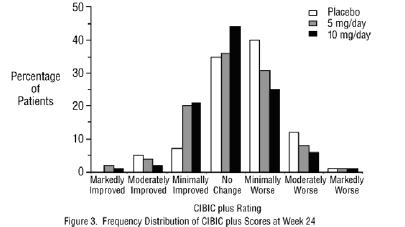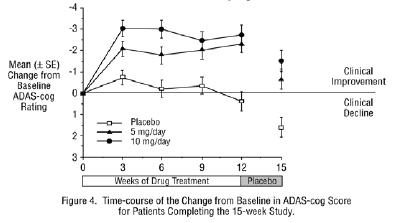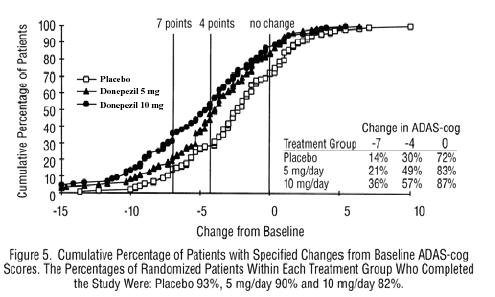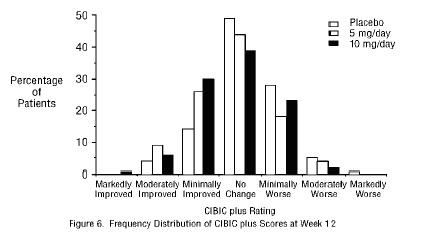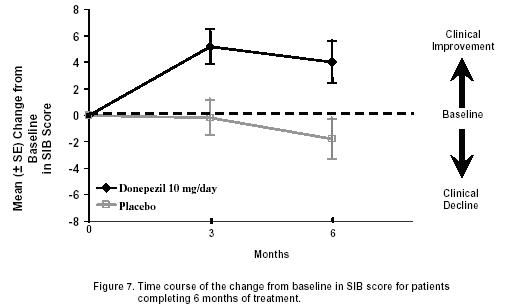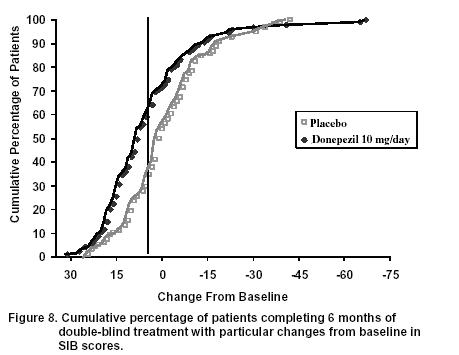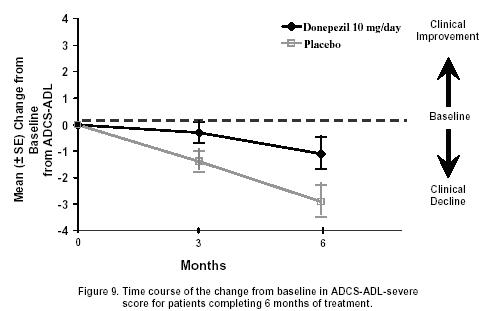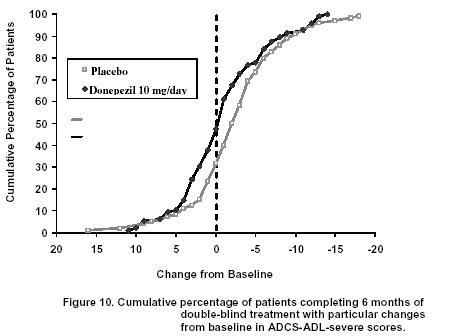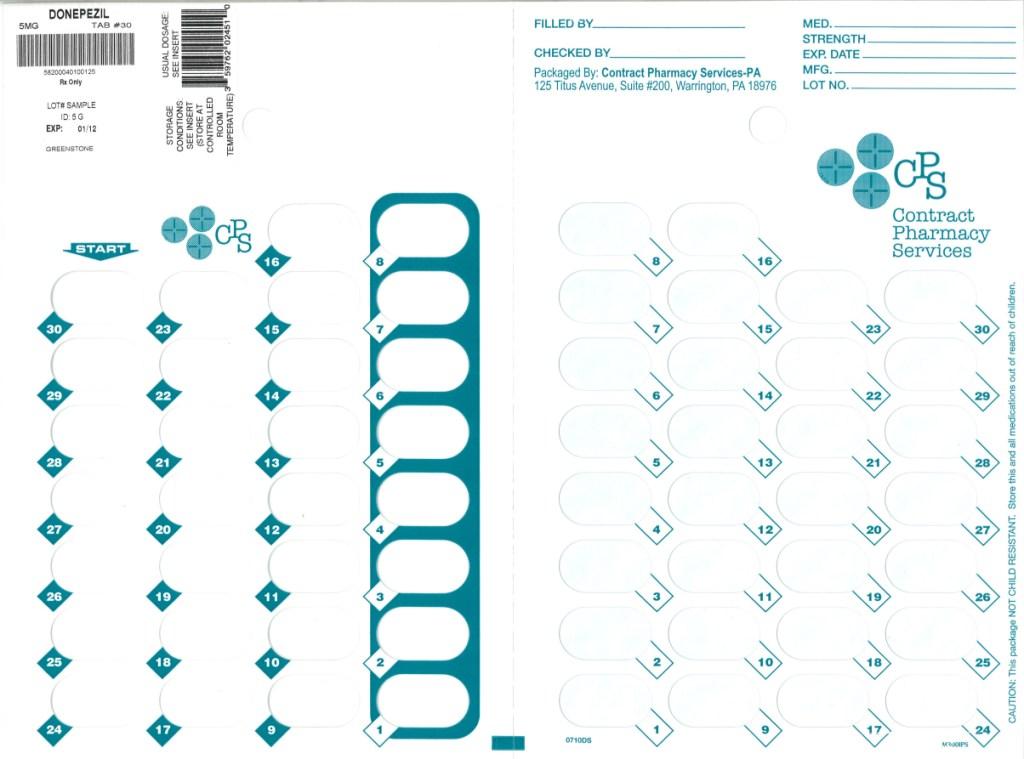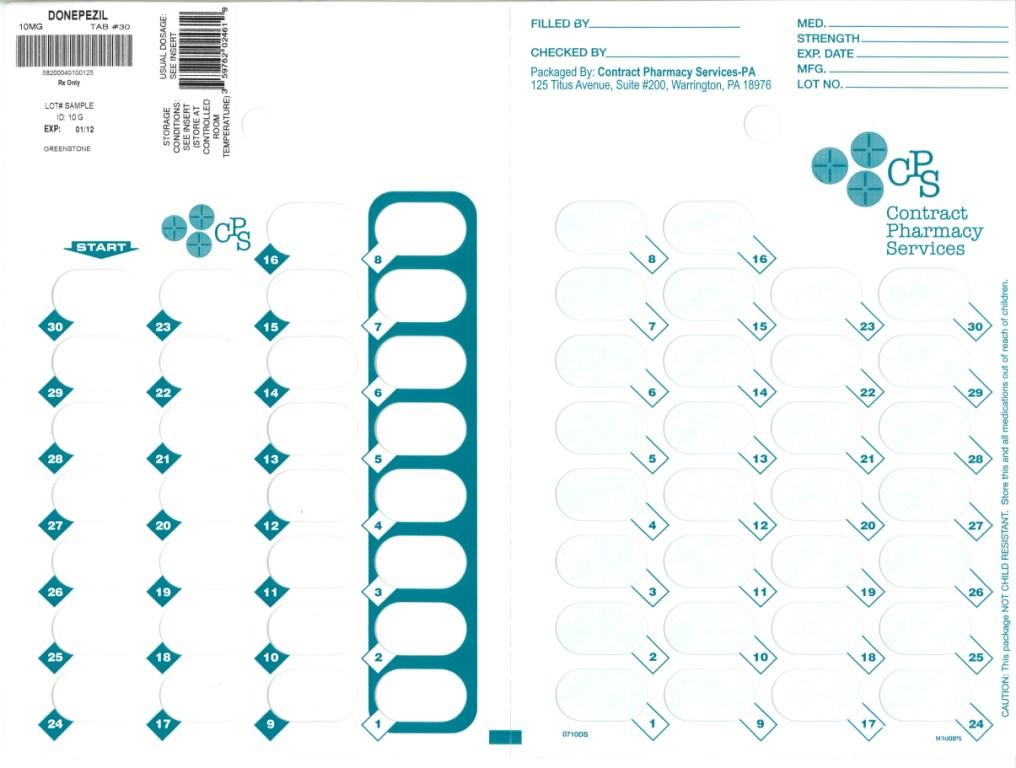 DRUG LABEL: Donepezil Hydrochloride
NDC: 67046-128 | Form: TABLET, FILM COATED
Manufacturer: Contract Pharmacy Services-PA
Category: prescription | Type: HUMAN PRESCRIPTION DRUG LABEL
Date: 20110131

ACTIVE INGREDIENTS: DONEPEZIL HYDROCHLORIDE 5 mg/1 1
INACTIVE INGREDIENTS: LACTOSE MONOHYDRATE; STARCH, CORN; CELLULOSE, MICROCRYSTALLINE; HYDROXYPROPYL CELLULOSE; MAGNESIUM STEARATE; TALC; POLYETHYLENE GLYCOL 8000; HYPROMELLOSES; TITANIUM DIOXIDE

HIGHLIGHTS OF PRESCRIBING INFORMATION

These highlights do not include all the information needed to use donepezil hydrochloride tablets safely and effectively. See full prescribing information for donepezil hydrochloride tablets.
Donepezil hydrochloride tablets
Initial U.S. Approval: 1996

RECENT MAJOR CHANGES

None

1 INDICATIONS AND USAGE

Donepezil hydrochloride tablets are indicated for the treatment of dementia of the Alzheimer’s type. Efficacy has been demonstrated in patients with mild, moderate, and severe Alzheimer’s Disease (1).

2 DOSAGE AND ADMINISTRATION

- Mild to Moderate Alzheimer’s disease - 5 mg or 10 mg administered once daily (2.1)
- Severe Alzheimer’s disease - 10 mg administered once daily (2.2)

A dose of 10 mg once daily can be administered once patients have been on a daily dose of 5 mg for 4 to 6 weeks. (2.3)

3 DOSAGE FORMS AND STRENGTHS

- Tablets: 5 mg and 10 mg (3)

4 CONTRAINDICATIONS

- Patients with known hypersensitivity to donepezil hydrochloride or to piperidine derivatives (4)

5 WARNINGS AND PRECAUTIONS

- Cholinesterase inhibitors are likely to exaggerate succinylcholine-type muscle relaxation during anesthesia (5.1).
- Cholinesterase inhibitors may have vagotonic effects on the sinoatrial and atrioventricular nodes manifesting as bradycardia or heart block (5.2).
- Donepezil hydrochloride can cause vomiting. Patients should be observed closely at initiation of treatment and after dose increases (5.3).
- Patients should be monitored closely for symptoms of active or occult gastrointestinal bleeding, especially those at increased risk for developing ulcers (5.4).
- Cholinomimetics may cause bladder outflow obstructions (5.6).
- Cholinomimetics are believed to have some potential to cause generalized convulsions (5.7).
- Cholinesterase inhibitors should be prescribed with care to patients with a history of asthma or obstructive pulmonary disease (5.8).

6 ADVERSE REACTIONS

The most common adverse reactions in clinical studies of donepezil hydrochloride are nausea, diarrhea, insomnia, vomiting, muscle cramps, fatigue, and anorexia (6.1).

To report SUSPECTED ADVERSE REACTIONS, contact the FDA at 1-800-FDA-1088 or www.fda.gov/medwatch.

7 DRUG INTERACTIONS

- Cholinesterase inhibitors have the potential to interfere with the activity of anticholinergic medications (7.3).
- A synergistic effect may be expected with concomitant administration of succinylcholine, similar neuromuscular blocking agents, or cholinergic agonists (7.4).

8 USE IN SPECIFIC POPULATIONS

- Based on animal data, donepezil hydrochloride may cause fetal harm (8.1).

FULL PRESCRIBING INFORMATION

1 INDICATIONS AND USAGE

Donepezil hydrochloride tablets are indicated for the treatment of dementia of the Alzheimer’s type. Efficacy has been demonstrated in patients with mild, moderate, and severe Alzheimer’s disease.

2 DOSAGE AND ADMINISTRATION

Donepezil hydrochloride tablets should be taken in the evening, just prior to retiring.

Donepezil hydrochloride tablets can be taken with or without food and should be swallowed whole with water. Donepezil hydrochloride tablets should not be split or crushed.

2.1. Mild to Moderate Alzheimer’s Disease

The dosages of donepezil hydrochloride tablets shown to be effective in controlled clinical trials are 5 mg and 10 mg administered once per day.

The higher dose of 10 mg did not provide a statistically significantly greater clinical benefit than 5 mg. There is a suggestion, however, based upon order of group mean scores and dose trend analyses of data from these clinical trials, that a daily dose of 10 mg of donepezil hydrochloride tablets might provide additional benefit for some patients. Accordingly, whether or not to employ a dose of 10 mg is a matter of prescriber and patient preference.

2.2. Severe Alzheimer’s Disease

Donepezil hydrochloride tablets have been shown to be effective in controlled clinical trials at a doses of 10 mg administered once daily.

2.3. Titration

The recommended starting dose of donepezil hydrochloride tablets is 5 mg once daily. Evidence from the controlled trials in mild to moderate Alzheimer’s disease indicates that the 10 mg dose, with a one week titration, is likely to be associated with a higher incidence of cholinergic adverse events compared to the 5 mg dose. In open-label trials using a 6 week titration, the type and frequency of these same adverse events were similar between the 5 mg and 10 mg dose groups. Therefore, because donepezil hydrochloride tablets steady state is achieved about 15 days after it is started and because the incidence of untoward effects may be influenced by the rate of dose escalation, a dose of 10 mg should not be administered until patients have been on a daily dose of 5 mg for 4 to 6 weeks.

3 DOSAGE FORMS AND STRENGTHS

Donepezil hydrochloride is supplied as film-coated, round tablets containing 5 mg, or 10 mg of donepezil hydrochloride.

The 5 mg tablets are white. The strength, in mg (5), is debossed on one side and a stylized G is debossed on the other side.

The 10 mg tablets are yellow. The strength, in my (10) is debossed on one side and a stylized G is debossed on the other side.

4 CONTRAINDICATIONS

Donepezil hydrochloride is contraindicated in patients with known hypersensitivity to donepezil hydrochloride or to piperidine derivatives.

5 WARNINGS AND PRECAUTIONS

5.1. Anesthesia

Donepezil hydrochloride, as a cholinesterase inhibitor, is likely to exaggerate succinylcholine-type muscle relaxation during anesthesia.

5.2. Cardiovascular Conditions

Because of their pharmacological action, cholinesterase inhibitors may have vagotonic effects on the sinoatrial and atrioventricular nodes. This effect may manifest as bradycardia or heart block in patients both with and without known underlying cardiac conduction abnormalities. Syncopal episodes have been reported in association with the use of donepezil hydrochloride.

5.3. Nausea and Vomiting

Donepezil hydrochloride, as a predictable consequence of its pharmacological properties, has been shown to produce diarrhea, nausea, and vomiting. These effects, when they occur, appear more frequently with the 10 mg/day dose than with the 5 mg/day dose.

Although in most cases, these effects have been mild and transient, sometimes lasting one to three weeks, and have resolved during continued use of donepezil hydrochloride, patients should be observed closely at the initiation of treatment and after dose increases.

5.4. Peptic Ulcer Disease and GI Bleeding

Through their primary action, cholinesterase inhibitors may be expected to increase gastric acid secretion due to increased cholinergic activity. Therefore, patients should be monitored closely for symptoms of active or occult gastrointestinal bleeding, especially those at increased risk for developing ulcers, e.g., those with a history of ulcer disease or those receiving concurrent nonsteroidal anti-inflammatory drugs (NSAIDs). Clinical studies of donepezil hydrochloride in a dose of 5 mg/day to 10 mg/day have shown no increase, relative to placebo, in the incidence of either peptic ulcer disease or gastrointestinal bleeding.

5.6 Genitourinary Conditions

Although not observed in clinical trials of donepezil hydrochloride, cholinomimetics may cause bladder outflow obstruction.

5.7 Neurological Conditions: Seizures

Cholinomimetics are believed to have some potential to cause generalized convulsions. However, seizure activity also may be a manifestation of Alzheimer’s disease.

5.8 Pulmonary Conditions

Because of their cholinomimetic actions, cholinesterase inhibitors should be prescribed with care to patients with a history of asthma or obstructive pulmonary disease.

6 ADVERSE REACTIONS

6.1. Clinical Studies Experience

Mild to Moderate Alzheimer’s Disease

Adverse Events Leading to Discontinuation

The rates of discontinuation from controlled clinical trials of donepezil hydrochloride due to adverse events for the donepezil hydrochloride 5 mg/day treatment groups were comparable to those of placebo treatment groups at approximately 5%. The rate of discontinuation of patients who received 7-day escalations from 5 mg/day to 10 mg/day was higher at 13%.

The most common adverse events leading to discontinuation, defined as those occurring in at least 2% of patients and at twice or more the incidence seen in placebo patients, are shown in Table 1.

Table 1. Most Frequent Adverse Events Leading to Withdrawal from Controlled Clinical Trials by Dose Group
Dose Group | Placebo | 5 mg/day Donepezil Hydrochloride | 10 mg/day Donepezil Hydrochloride
Patients Randomized | 355 | 350 | 315
Event/%Discontinuing
Nausea | 1% | 1% | 3%
Diarrhea | 0% | < 1% | 3%
Vomiting | < 1% | < 1% | 2%

Most Frequent Adverse Events Seen in Association with the Use of Donepezil Hydrochloride

The most common adverse events, defined as those occurring at a frequency of at least 5% in patients receiving 10 mg/day and twice the placebo rate, are largely predicted by donepezil hydrochloride’s cholinomimetic effects. These include nausea, diarrhea, insomnia, vomiting, muscle cramp, fatigue and anorexia. These adverse events were often of mild intensity and transient, resolving during continued donepezil hydrochloride treatment without the need for dose modification.

There is evidence to suggest that the frequency of these common adverse events may be affected by the rate of titration. An open-label study was conducted with 269 patients who received placebo in the 15 and 30-week studies. These patients were titrated to a dose of 10 mg/day over a 6-week period. The rates of common adverse events were lower than those seen in patients titrated to 10 mg/day over one week in the controlled clinical trials and were comparable to those seen in patients on 5 mg/day.

See Table 2 for a comparison of the most common adverse events following one and six week titration regimens.

Table 2. Comparison of Rates of Adverse Events in Mild to Moderate Patients Titrated to 10 mg/day over 1 and 6 Weeks
 | No titration |  | One week titration | Six week titration
Adverse Event | Placebo (n = 315) | 5 mg/day (n = 311) | 10 mg/day (n = 315) | 10 mg/day (n = 269)
Nausea | 6% | 5% | 19% | 6%
Diarrhea | 5% | 8% | 15% | 9%
Insomnia | 6% | 6% | 14% | 6%
Fatigue | 3% | 4% | 8% | 3%
Vomiting | 3% | 3% | 8% | 5%
Muscle cramps | 2% | 6% | 8% | 3%
Anorexia | 2% | 3% | 7% | 3%

Adverse Events Reported in Controlled Trials

The events cited reflect experience gained under closely monitored conditions of clinical trials in a highly selected patient population. In actual clinical practice or in other clinical trials, these frequency estimates may not apply, as the conditions of use, reporting behavior, and the kinds of patients treated may differ. Table 3 lists treatment emergent signs and symptoms that were reported in at least 2% of patients in placebo-controlled trials who received donepezil hydrochloride and for which the rate of occurrence was greater for patients treated with donepezil hydrochloride than with placebo. In general, adverse events occurred more frequently in female patients and with advancing age.

Table 3. Adverse Events Reported in Controlled Clinical Trials in Mild to Moderate Alzheimer’s Disease in at Least 2% of Patients Receiving Donepezil Hydrochloride and at a Higher Frequency than Placebo Treated Patients
Body System/Adverse Event | Placebo (n = 355) | Donepezil Hydrochloride (n = 747)
Percent of Patients with any Adverse Event | 72 | 74
Body as a Whole
Headache | 9 | 10
Pain, various locations | 8 | 9
Accident | 6 | 7
Fatigue | 3 | 5
Cardiovascular System
Syncope | 1 | 2
Digestive System
Nausea | 6 | 11
Diarrhea | 5 | 10
Vomiting | 3 | 5
Anorexia | 2 | 4
Hemic and Lymphatic System
Ecchymosis | 3 | 4
Metabolic and Nutritional Systems
Weight Decrease | 1 | 3
Musculoskeletal System
Muscle Cramps | 2 | 6
Arthritis | 1 | 2
Nervous System
Insomnia | 6 | 9
Dizziness | 6 | 8
Depression | < 1 | 3
Abnormal Dreams | 0 | 3
Somnolence | < 1 | 2
Urogenital System
Frequent Urination | 1 | 2

Other Adverse Events Observed During Clinical Trials

Donepezil hydrochloride has been administered to over 1700 individuals during clinical trials worldwide. Approximately 1200 of these patients have been treated for at least 3 months and more than 1000 patients have been treated for at least 6 months. Controlled and uncontrolled trials in the United States included approximately 900 patients. In regards to the highest dose of 10 mg/day, this population includes 650 patients treated for 3 months, 475 patients treated for 6 months and 116 patients treated for over 1 year. The range of patient exposure is from 1 to 1214 days.

Treatment emergent signs and symptoms that occurred during three controlled clinical trials and two open-label trials in the United States were recorded as adverse events by the clinical investigators using terminology of their own choosing. To provide an overall estimate of the proportion of individuals having similar types of events, the events were grouped into a smaller number of standardized categories using a modified COSTART dictionary, and event frequencies were calculated across all studies. These categories are used in the listing below. The frequencies represent the proportion of 900 patients from these trials who experienced that event while receiving donepezil hydrochloride. All adverse events occurring at least twice are included, except for those already listed in Tables 2 or 3, COSTART terms too general to be informative, or events less likely to be drug related. Events are classified by body system and listed using the following definitions: Frequent adverse events - those occurring in at least 1/100 patients; Infrequent adverse events - those occurring in 1/100 to 1/1000 patients. These adverse events are not necessarily related to donepezil hydrochloride treatment and in most cases were observed at a similar frequency in placebo treated patients in the controlled studies. No important additional adverse events were seen in studies conducted outside the United States.

Body as a Whole: Frequent: influenza, chest pain, toothache; Infrequent: fever, edema face, periorbital edema, hernia hiatal, abscess, cellulitis, chills, generalized coldness, head fullness, listlessness.

Cardiovascular System: Frequent: hypertension, vasodilation, atrial fibrillation, hot flashes, hypotension; Infrequent: angina pectoris, postural hypotension, myocardial infarction, AV block (first degree), congestive heart failure, arteritis, bradycardia, peripheral vascular disease, supraventricular tachycardia, deep vein thrombosis.

Digestive System: Frequent: fecal incontinence, gastrointestinal bleeding, bloating, epigastric pain; Infrequent: eructation, gingivitis, increased appetite, flatulence, periodontal abscess, cholelithiasis, diverticulitis, drooling, dry mouth, fever sore, gastritis, irritable colon, tongue edema, epigastric distress, gastroenteritis, increased transaminases, hemorrhoids, ileus, increased thirst, jaundice, melena, polydipsia, duodenal ulcer, stomach ulcer.

Endocrine System: Infrequent: diabetes mellitus, goiter.

Hemic and Lymphatic System: Infrequent: anemia, thrombocythemia, thrombocytopenia, eosinophilia, erythrocytopenia.

Metabolic and Nutritional Disorders: Frequent: dehydration; Infrequent: gout, hypokalemia, increased creatine kinase, hyperglycemia, weight increase, increased lactate dehydrogenase.

Musculoskeletal System: Frequent: bone fracture; Infrequent: muscle weakness, muscle fasciculation.

Nervous System: Frequent: delusions, tremor, irritability, paresthesia, aggression, vertigo, ataxia, increased libido, restlessness, abnormal crying, nervousness, aphasia; Infrequent: cerebrovascular accident, intracranial hemorrhage, transient ischemic attack, emotional lability, neuralgia, coldness (localized), muscle spasm, dysphoria, gait abnormality, hypertonia, hypokinesia, neurodermatitis, numbness (localized), paranoia, dysarthria, dysphasia, hostility, decreased libido, melancholia, emotional withdrawal, nystagmus, pacing.

Respiratory System: Frequent: dyspnea, sore throat, bronchitis; Infrequent: epistaxis, post nasal drip, pneumonia, hyperventilation, pulmonary congestion, wheezing, hypoxia, pharyngitis, pleurisy, pulmonary collapse, sleep apnea, snoring.

Skin and Appendages: Frequent: pruritus, diaphoresis, urticaria; Infrequent: dermatitis, erythema, skin discoloration, hyperkeratosis, alopecia, fungal dermatitis, herpes zoster, hirsutism, skin striae, night sweats, skin ulcer.

Special Senses: Frequent: cataract, eye irritation, vision blurred; Infrequent: dry eyes, glaucoma, earache, tinnitus, blepharitis, decreased hearing, retinal hemorrhage, otitis externa, otitis media, bad taste, conjunctival hemorrhage, ear buzzing, motion sickness, spots before eyes.

Urogenital System: Frequent: urinary incontinence, nocturia; Infrequent: dysuria, hematuria, urinary urgency, metrorrhagia, cystitis, enuresis, prostate hypertrophy, pyelonephritis, inability to empty bladder, breast fibroadenosis, fibrocystic breast, mastitis, pyuria, renal failure, vaginitis.

Severe Alzheimer’s Disease

Adverse Events Leading to Discontinuation

The rates of discontinuation from controlled clinical trials of donepezil hydrochloride due to adverse events for the donepezil hydrochloride patients were approximately 12% compared to 7% for placebo patients. The most common adverse events leading to discontinuation, defined as those occurring in at least 2% of donepezil hydrochloride patients and at twice or more the incidence seen in placebo, were anorexia (2% vs. 1% placebo), nausea (2% vs. < 1% placebo), diarrhea (2% vs. 0% placebo) and urinary tract infection (2% vs. 1% placebo).

Most Frequent Adverse Events Seen in Association with the Use of Donepezil Hydrochloride

The most common adverse events, defined as those occurring at a frequency of at least 5% in patients receiving donepezil hydrochloride and at twice or more the placebo rate, are largely predicted by donepezil hydrochloride‘s cholinomimetic effects. These include diarrhea, anorexia, vomiting, nausea, and ecchymosis. These adverse events were often of mild intensity and transient, resolving during continued donepezil hydrochloride treatment without the need for dose modification.

Adverse Events Reported in Controlled Trials

Table 4 lists adverse events that were reported in at least 2% of patients in placebo-controlled trials who received donepezil hydrochloride and for which the rate of occurrence was greater for patients treated with donepezil hydrochloride than with placebo.

Table 4. Adverse Events Reported in Controlled Clinical Trials in Severe Alzheimer’s Disease in at Least 2% of Patients Receiving Donepezil Hydrochloride and at a Higher Frequency than Placebo Treated Patients
Body System/Adverse Event | Placebo (n = 392) | Donepezil Hydrochloride (n = 501)
Percent of Patients with any Adverse Event | 73 | 81
Body as a Whole
Accident | 12 | 13
Infection | 9 | 11
Headache | 3 | 4
Pain | 2 | 3
Back Pain | 2 | 3
Fever | 1 | 2
Chest Pain | < 1 | 2
Cardiovascular System
Hypertension | 2 | 3
Hemorrhage | 1 | 2
Syncope | 1 | 2
Digestive System
Diarrhea | 4 | 10
Vomiting | 4 | 8
Anorexia | 4 | 8
Nausea | 2 | 6
Hemic and Lymphatic System
Ecchymosis | 2 | 5
Metabolic and Nutritional Systems
Creatine Phosphokinase Increased | 1 | 3
Dehydration | 1 | 2
Hyperlipemia | < 1 | 2
Nervous System
Insomnia | 4 | 5
Hostility | 2 | 3
Nervousness | 2 | 3
Hallucinations | 1 | 3
Somnolence | 1 | 2
Dizziness | 1 | 2
Depression | 1 | 2
Confusion | 1 | 2
Emotional Lability | 1 | 2
Personality Disorder | 1 | 2
Skin And Appendages
Eczema | 2 | 3
Urogenital System
Urinary Incontinence | 1 | 2

Other Adverse Events Observed During Clinical Trials

Donepezil hydrochloride has been administered to over 600 patients with severe Alzheimer’s disease during clinical trials of at least 6 months duration, including three double-blind placebo-controlled trials, two of which had an open label extension. All adverse events occurring at least twice are included, except for those already listed in Table 4, COSTART terms too general to be informative, or events less likely to be drug related. Events are classified by body system using the COSTART dictionary and listed using the following definitions: Frequent adverse events - those occurring in at least 1/100 patients; Infrequent adverse events - those occurring in 1/100 to 1/1000 patients. These adverse events are not necessarily related to donepezil hydrochloride treatment and in most cases were observed at a similar frequency in placebo treated patients in the controlled studies.

Body as a Whole: Frequent: abdominal pain, asthenia, fungal infection, flu syndrome; Infrequent: allergic reaction, cellulitis, malaise, sepsis, face edema, hernia.

Cardiovascular System: Frequent: hypotension, bradycardia, ECG abnormal, heart failure; Infrequent: myocardial infarction, angina pectoris, atrial fibrillation, congestive heart failure, peripheral vascular disorder, supraventricular extrasystoles, ventricular extrasystoles, cardiomegaly.

Digestive System: Frequent: constipation, gastroenteritis, fecal incontinence, dyspepsia; Infrequent: gamma glutamyl transpeptidase increase, gastritis, dysphagia, periodontitis, stomach ulcer, periodontal abscess, flatulence, liver function tests abnormal, eructation, esophagitis, rectal hemorrhage.

Endocrine System: Infrequent: diabetes mellitus.

Hemic and Lymphatic System: Frequent: anemia; Infrequent: leukocytosis.

Metabolic and Nutritional Disorders: Frequent: weight loss, peripheral edema, edema, lactic dehydrogenase increased, alkaline phosphatase increased; Infrequent: hypercholesteremia, hypokalemia, hypoglycemia, weight gain, bilirubinemia, BUN increased, B12 deficiency anemia, cachexia, creatinine increased, gout, hyponatremia, hypoproteinemia, iron deficiency anemia, SGOT increased, SGPT increased.

Musculoskeletal System: Frequent: arthritis; Infrequent: arthrosis, bone fracture, arthralgia, leg cramps, osteoporosis, myalgia.

Nervous System: Frequent: agitation, anxiety, tremor, convulsion, wandering, abnormal gait; Infrequent: apathy, vertigo, delusions, abnormal dreams, cerebrovascular accident, increased salivation, ataxia, euphoria, vasodilatation, cerebral hemorrhage, cerebral infarction, cerebral ischemia, dementia, extrapyramidal syndrome, grand mal convulsion, hemiplegia, hypertonia, hypokinesia.

Respiratory System: Frequent: pharyngitis, pneumonia, cough increased, bronchitis; Infrequent: dyspnea, rhinitis, asthma.

Skin and Appendages: Frequent: rash, skin ulcer, pruritus; Infrequent: psoriasis, skin discoloration, herpes zoster, dry skin, sweating, urticaria, vesiculobullous rash.

Special Senses: Infrequent: conjunctivitis, glaucoma, abnormal vision, ear pain, lacrimation disorder.

Urogenital System: Frequent: urinary tract infection, cystitis, hematuria, glycosuria; Infrequent: vaginitis, dysuria, urinary frequency, albuminuria.

6.2 Postmarketing Experience

Voluntary reports of adverse events temporally associated with donepezil hydrochloride that have been received since market introduction that are not listed above, and for which there are inadequate data to determine the causal relationship with the drug include the following: abdominal pain, agitation, cholecystitis, confusion, convulsions, hallucinations, heart block (all types), hemolytic anemia, hepatitis, hyponatremia, neuroleptic malignant syndrome, pancreatitis, and rash.

7 DRUG INTERACTIONS

7.1. Effect of Donepezil Hydrochloride on the Metabolism of Other Drugs

No in vivo clinical trials have investigated the effect of donepezil hydrochloride on the clearance of drugs metabolized by CYP 3A4 (e.g. cisapride, terfenadine) or by CYP 2D6 (e.g. imipramine). However, in vitro studies show a low rate of binding to these enzymes (mean Ki about 50 to 130 μM), that, given the therapeutic plasma concentrations of donepezil (164 nM), indicates little likelihood of interference.

Whether donepezil hydrochloride has any potential for enzyme induction is not known. Formal pharmacokinetic studies evaluated the potential of donepezil hydrochloride for interaction with theophylline, cimetidine, warfarin, digoxin and ketoconazole. No effects of donepezil hydrochloride on the pharmacokinetics of these drugs were observed.

7.2. Effect of Other Drugs on the Metabolism of Donepezil Hydrochloride

Ketoconazole and quinidine, inhibitors of CYP450, 3A4 and 2D6, respectively, inhibit donepezil metabolism in vitro. Whether there is a clinical effect of quinidine is not known. In a 7-day crossover study in 18 healthy volunteers, ketoconazole (200 mg q.d.) increased mean donepezil (5 mg q.d.) concentrations (AUC0-24 and Cmax) by 36%. The clinical relevance of this increase in concentration is unknown.

A small effect of CYP2D6 inhibitors was identified in a population pharmacokinetic analysis of plasma donepezil concentrations measured in patients with Alzheimer’s disease. Donepezil clearance was reduced by approximately 17% in patients taking 10 mg in combination with a known CYP2D6 inhibitor. This result is consistent with the conclusion that CYP2D6 is a minor metabolic pathway of donepezil.

Inducers of CYP 2D6 and CYP 3A4 (e.g., phenytoin, carbamazepine, dexamethasone, rifampin, and phenobarbital) could increase the rate of elimination of donepezil hydrochloride.

Formal pharmacokinetic studies demonstrated that the metabolism of donepezil hydrochloride is not significantly affected by concurrent administration of digoxin or cimetidine.

7.3. Use with Anticholinergics

Because of their mechanism of action, cholinesterase inhibitors have the potential to interfere with the activity of anticholinergic medications.

7.4. Use with Cholinomimetics and Other Cholinesterase Inhibitors

A synergistic effect may be expected when cholinesterase inhibitors are given concurrently with succinylcholine, similar neuromuscular blocking agents or cholinergic agonists such as bethanechol.

8 USE IN SPECIFIC POPULATIONS

8.1 Pregnancy

Pregnancy Category C: There are no adequate or well-controlled studies in pregnant women. Donepezil hydrochloride should be used during pregnancy only if the potential benefit justifies the potential risk to the fetus.

Oral administration of donepezil to pregnant rats and rabbits during the period of organogenesis did not produce any teratogenic effects at doses up to 16 mg/kg/day (approximately 16 times the maximum recommended human dose [MRHD] of 10 mg/day on a mg/m ^2 basis) and 10 mg/kg/day (approximately 20 times the MRHD on a mg/m^2 basis), respectively. Oral administration of donepezil (1, 3, 10 mg/kg/day) to rats during late gestation and throughout lactation to weaning produced an increase in stillbirths and reduced offspring survival through postpartum day 4 at the highest dose. The no-effect dose of 3 mg/kg/day is approximately 3 times the MRHD on a mg/m^2 basis.

8.3 Nursing Mothers

It is not known whether donepezil is excreted in human breast milk. Caution should be exercised when donepezil hydrochloride is administered to a nursing woman.

8.4 Pediatric Use

The safety and effectiveness of donepezil hydrochloride in children have not been established.

8.5 Geriatric Use

Alzheimer’s disease is a disorder occurring primarily in individuals over 55 years of age. The mean age of patients enrolled in the clinical studies with donepezil hydrochloride was 73 years; 80% of these patients were between 65 and 84 years old, and 49% of patients were at or above the age of 75. The efficacy and safety data presented in the clinical trials section were obtained from these patients. There were no clinically significant differences in most adverse events reported by patient groups ≥ 65 years old and < 65 years old.

10 OVERDOSAGE

Because strategies for the management of overdose are continually evolving, it is advisable to contact a Poison Control Center to determine the latest recommendations for the management of an overdose of any drug.

As in any case of overdose, general supportive measures should be utilized. Overdosage with cholinesterase inhibitors can result in cholinergic crisis characterized by severe nausea, vomiting, salivation, sweating, bradycardia, hypotension, respiratory depression, collapse and convulsions. Increasing muscle weakness is a possibility and may result in death if respiratory muscles are involved. Tertiary anticholinergics such as atropine may be used as an antidote for donepezil hydrochloride overdosage. Intravenous atropine sulfate titrated to effect is recommended: an initial dose of 1 to 2 mg IV with subsequent doses based upon clinical response. Atypical responses in blood pressure and heart rate have been reported with other cholinomimetics when co-administered with quaternary anticholinergics such as glycopyrrolate. It is not known whether donepezil hydrochloride and/or its metabolites can be removed by dialysis (hemodialysis, peritoneal dialysis, or hemofiltration).

Dose-related signs of toxicity in animals included reduced spontaneous movement, prone position, staggering gait, lacrimation, clonic convulsions, depressed respiration, salivation, miosis, tremors, fasciculation and lower body surface temperature.

11 DESCRIPTION

Donepezil hydrochloride is a reversible inhibitor of the enzyme acetylcholinesterase, known chemically as (±)-2, 3-dihydro-5, 6-dimethoxy-2-[[1-(phenylmethyl)-4-piperidinyl]methyl]-1 H-inden-1-one hydrochloride. Donepezil hydrochloride is commonly referred to in the pharmacological literature as E2020. It has a molecular formula of C24H29NO3HCl and a molecular weight of 415.96. Donepezil hydrochloride is a white to off-white crystalline powder and is soluble in chloroform, sparingly soluble in water, methanol and acetic acid.

Donepezil hydrochloride is available for oral administration in film-coated tablets containing 5, or 10 mg of donepezil hydrochloride.

Inactive ingredients in 5 mg and 10 mg tablets are lactose monohydrate, corn starch, microcrystalline cellulose, hydroxypropyl cellulose, and magnesium stearate. The film coating contains talc, polyethylene glycol, hypromellose and titanium dioxide. Additionally, the 10 mg tablet contains yellow iron oxide (synthetic) as a coloring agent.

12 CLINICAL PHARMACOLOGY

12.1 Mechanism of Action

Current theories on the pathogenesis of the cognitive signs and symptoms of Alzheimer’s disease attribute some of them to a deficiency of cholinergic neurotransmission.

Donepezil hydrochloride is postulated to exert its therapeutic effect by enhancing cholinergic function. This is accomplished by increasing the concentration of acetylcholine through reversible inhibition of its hydrolysis by acetylcholinesterase. There is no evidence that donepezil alters the course of the underlying dementing process.

12.3 Pharmacokinetics

Pharmacokinetics of donepezil are linear over a dose range of 1 to 10 mg given once daily. The rate and extent of absorption of donepezil hydrochloride tablets are not influenced by food.

Based on population pharmacokinetic analysis of plasma donepezil concentrations measured in patients with Alzheimer’s disease, following oral dosing, peak plasma concentration is achieved in 3 hours for donepezil hydrochloride 10 mg tablets.

The elimination half life of donepezil is about 70 hours, and the mean apparent plasma clearance (Cl/F) is 0.13 to 0.19 L/hr/kg. Following multiple dose administration, donepezil accumulates in plasma by 4 to 7 fold, and steady state is reached within 15 days. The steady state volume of distribution is 12 to 16 L/kg. Donepezil is approximately 96% bound to human plasma proteins, mainly to albumins (about 75%) and alpha 1 - acid glycoprotein (about 21%) over the concentration range of 2 to 1000 ng/mL.

Donepezil is both excreted in the urine intact and extensively metabolized to four major metabolites, two of which are known to be active, and a number of minor metabolites, not all of which have been identified. Donepezil is metabolized by CYP 450 isoenzymes 2D6 and 3A4 and undergoes glucuronidation. Following administration of ^14C-labeled donepezil, plasma radioactivity, expressed as a percent of the administered dose, was present primarily as intact donepezil (53%) and as 6-O-desmethyl donepezil (11%), which has been reported to inhibit AChE to the same extent as donepezil in vitro and was found in plasma at concentrations equal to about 20% of donepezil. Approximately 57% and 15% of the total radioactivity was recovered in urine and feces, respectively, over a period of 10 days, while 28% remained unrecovered, with about 17% of the donepezil dose recovered in the urine as unchanged drug. Examination of the effect of CYP2D6 genotype in Alzheimer’s patients showed differences in clearance values among CYP2D6 genotype subgroups. When compared to the extensive metabolizers, poor metabolizers had a 31.5% slower clearance and ultra-rapid metabolizers had a 24% faster clearance. These results suggest CYP2D6 has a minor role in the metabolism of donepezil.

Hepatic Disease: In a study of 10 patients with stable alcoholic cirrhosis, the clearance of donepezil hydrochloride was decreased by 20% relative to 10 healthy age- and sex-matched subjects.

Renal Disease: In a study of 11 patients with moderate to severe renal impairment(ClC < 18 mL/min/1.73 m^2) the clearance of donepezil hydrochloride did not differ from 11 age- and sex-matched healthy subjects.

Age: No formal pharmacokinetic study was conducted to examine age-related differences in the pharmacokinetics of donepezil hydrochloride. Population pharmacokinetic analysis suggested that the clearance of donepezil in patients decreases with increasing age. When compared with 65-year old, subjects, 90-year old subjects have a 17% decrease in clearance, while 40-year old subjects have a 33% increase in clearance. The effect of age on donepezil clearance may not be clinically significant.

Gender and Race: No specific pharmacokinetic study was conducted to investigate the effects of gender and race on the disposition of donepezil hydrochloride. However, retrospective pharmacokinetic analysis and population pharmacokinetic analysis of plasma donepezil concentrations measured in patients with Alzheimer’s disease indicates that gender and race (Japanese and Caucasians) did not affect the clearance of donepezil hydrochloride to an important degree.

Body weight: There was a relationship noted between body weight and clearance. Over the range of body weight from 50 kg to 110 kg, clearance increased from 7.77 L/h to 14.04 L/h, with a value of 10 L/hr for 70 kg individuals.

Drugs Highly Bound to Plasma Proteins: Drug displacement studies have been performed in vitro between this highly bound drug (96%) and other drugs such as furosemide, digoxin, and warfarin. Donepezil hydrochloride at concentrations of 0.3 to 10 micrograms/mL did not affect the binding of furosemide (5 micrograms/mL), digoxin (2 ng/mL), and warfarin (3 micrograms/mL) to human albumin. Similarly, the binding of donepezil hydrochloride to human albumin was not affected by furosemide, digoxin and warfarin.

13 NONCLINICAL TOXICOLOGY

13.1 Carcinogenesis, Mutagenesis, Impairment of Fertility

No evidence of a carcinogenic potential was obtained in an 88-week carcinogenicity study of donepezil hydrochloride conducted in CD-1 mice at doses up to 180 mg/kg/day (approximately 90 times the maximum recommended human dose on a mg/m ^2 basis), or in a 104-week carcinogenicity study in Sprague-Dawley rats at doses up to 30 mg/kg/day (approximately 30 times the maximum recommended human dose on a mg/m^2 basis).

Donepezil was not mutagenic in the Ames reverse mutation assay in bacteria, or in a mouse lymphoma forward mutation assay in vitro. In the chromosome aberration test in cultures of Chinese hamster lung (CHL) cells, some clastogenic effects were observed. Donepezil was not clastogenic in the in vivo mouse micronucleus test and was not genotoxic in an in vivo unscheduled DNA synthesis assay in rats.

Donepezil had no effect on fertility in rats at doses up to 10 mg/kg/day (approximately 8 times the maximum recommended human dose on a mg/m ^2 basis).

14 CLINICAL STUDIES

The effectiveness of donepezil hydrochloride as a treatment for Alzheimer’s disease is demonstrated by the results of randomized, double-blind, placebo-controlled clinical investigations.

14.1 Mild to Moderate Alzheimer’s Disease

The effectiveness of donepezil hydrochloride as a treatment for mild to moderate Alzheimer’s disease is demonstrated by the results of two randomized, double-blind, placebo-controlled clinical investigations in patients with Alzheimer’s disease (diagnosed by NINCDS and DSM III-R criteria, Mini-Mental State Examination ≥ 10 and ≤ 26 and Clinical Dementia Rating of 1 or 2). The mean age of patients participating in donepezil hydrochloride trials was 73 years with a range of 50 to 94. Approximately 62% of patients were women and 38% were men. The racial distribution was white 95%, black 3% and other races 2%.

Study Outcome Measures: In each study, the effectiveness of treatment with donepezil hydrochloride was evaluated using a dual outcome assessment strategy.

The ability of donepezil hydrochloride to improve cognitive performance was assessed with the cognitive subscale of the Alzheimer’s Disease Assessment Scale (ADAS-cog), a multi-item instrument that has been extensively validated in longitudinal cohorts of Alzheimer’s disease patients. The ADAS-cog examines selected aspects of cognitive performance including elements of memory, orientation, attention, reasoning, language and praxis. The ADAS-cog scoring range is from 0 to 70, with higher scores indicating greater cognitive impairment. Elderly normal adults may score as low as 0 or 1, but it is not unusual for non-demented adults to score slightly higher.

The patients recruited as participants in each study had mean scores on the ADAS-cog of approximately 26 points, with a range from 4 to 61. Experience based on longitudinal studies of ambulatory patients with mild to moderate Alzheimer’s disease suggest that scores on the ADAS-cog increase (worsen) by 6 to 12 points per year. However, smaller changes may be seen in patients with very mild or very advanced disease since the ADAS-cog is not uniformly sensitive to change over the course of the disease. The annualized rate of decline in the placebo patients participating in donepezil hydrochloride trials was approximately 2 to 4 points per year.

The ability of donepezil hydrochloride to produce an overall clinical effect was assessed using a Clinician’s Interview-Based Impression of Change that required the use of caregiver information, the CIBIC-plus. The CIBIC-plus is not a single instrument and is not a standardized instrument like the ADAS-cog. Clinical trials for investigational drugs have used a variety of CIBIC formats, each different in terms of depth and structure.

As such, results from a CIBIC-plus reflect clinical experience from the trial or trials in which it was used and cannot be compared directly with the results of CIBIC-plus evaluations from other clinical trials. The CIBIC-plus used in donepezil hydrochloride trials was a semi-structured instrument that was intended to examine four major areas of patient function: General, Cognitive, Behavioral and Activities of Daily Living. It represents the assessment of a skilled clinician based upon his/her observations at an interview with the patient, in combination with information supplied by a caregiver familiar with the behavior of the patient over the interval rated. The CIBIC-plus is scored as a seven point categorical rating, ranging from a score of 1, indicating “markedly improved,” to a score of 4, indicating “no change” to a score of 7, indicating “markedly worse.” The CIBIC-plus has not been systematically compared directly to assessments not using information from caregivers (CIBIC) or other global methods.

Thirty-Week Study

In a study of 30 weeks duration, 473 patients were randomized to receive single daily doses of placebo, 5 mg/day or 10 mg/day of donepezil hydrochloride. The 30-week study was divided into a 24-week double-blind active treatment phase followed by a 6-week single-blind placebo washout period. The study was designed to compare 5 mg/day or 10 mg/day fixed doses of donepezil hydrochloride to placebo. However, to reduce the likelihood of cholinergic effects, the 10 mg/day treatment was started following an initial 7-day treatment with 5 mg/day doses.

Effects on the ADAS-cog: Figure 1 illustrates the time course for the change from baseline in ADAS-cog scores for all three dose groups over the 30 weeks of the study. After 24 weeks of treatment, the mean differences in the ADAS-cog change scores for donepezil hydrochloride treated patients compared to the patients on placebo were 2.8 and 3.1 points for the 5 mg/day and 10 mg/day treatments, respectively. These differences were statistically significant. While the treatment effect size may appear to be slightly greater for the 10 mg/day treatment, there was no statistically significant difference between the two active treatments.

Following 6 weeks of placebo washout, scores on the ADAS-cog for both the donepezil hydrochloride treatment groups were indistinguishable from those patients who had received only placebo for 30 weeks. This suggests that the beneficial effects of donepezil hydrochloride abate over 6 weeks following discontinuation of treatment and do not represent a change in the underlying disease. There was no evidence of a rebound effect 6 weeks after abrupt discontinuation of therapy.

Figure 2 illustrates the cumulative percentages of patients from each of the three treatment groups who had attained the measure of improvement in ADAS-cog score shown on the X axis. Three change scores, (7-point and 4-point reductions from baseline or no change in score) have been identified for illustrative purposes, and the percent of patients in each group achieving that result is shown in the inset table.

The curves demonstrate that both patients assigned to placebo and donepezil hydrochloride have a wide range of responses, but that the active treatment groups are more likely to show greater improvements. A curve for an effective treatment would be shifted to the left of the curve for placebo, while an ineffective or deleterious treatment would be superimposed upon or shifted to the right of the curve for placebo.

Effects on the CIBIC-plus: Figure 3 is a histogram of the frequency distribution of CIBIC-plus scores attained by patients assigned to each of the three treatment groups who completed 24 weeks of treatment. The mean drug-placebo differences for these groups of patients were 0.35 points and 0.39 points for 5 mg/day and 10 mg/day of donepezil hydrochloride, respectively. These differences were statistically significant. There was no statistically significant difference between the two active treatments.

Fifteen-Week Study

In a study of 15 weeks duration, patients were randomized to receive single daily doses of placebo or either 5 mg/day or 10 mg/day of donepezil hydrochloride for 12 weeks, followed by a 3-week placebo washout period. As in the 30-week study, to avoid acute cholinergic effects, the 10 mg/day treatment followed an initial 7-day treatment with 5 mg/day doses.

Effects on the ADAS-Cog: Figure 4 illustrates the time course of the change from baseline in ADAS-cog scores for all three dose groups over the 15 weeks of the study. After 12 weeks of treatment, the differences in mean ADAS-cog change scores for the donepezil hydrochloride treated patients compared to the patients on placebo were 2.7 and 3 points each, for the 5 and 10 mg/day donepezil hydrochloride treatment groups, respectively. These differences were statistically significant. The effect size for the 10 mg/day group may appear to be slightly larger than that for 5 mg/day. However, the differences between active treatments were not statistically significant.

Following 3 weeks of placebo washout, scores on the ADAS-cog for both the donepezil hydrochloride treatment groups increased, indicating that discontinuation of donepezil hydrochloride resulted in a loss of its treatment effect. The duration of this placebo washout period was not sufficient to characterize the rate of loss of the treatment effect, but, the 30-week study (see above) demonstrated that treatment effects associated with the use of donepezil hydrochloride abate within 6 weeks of treatment discontinuation.

Figure 5 illustrates the cumulative percentages of patients from each of the three treatment groups who attained the measure of improvement in ADAS-cog score shown on the X axis. The same three change scores, (7-point and 4-point reductions from baseline or no change in score) as selected for the 30-week study have been used for this illustration. The percentages of patients achieving those results are shown in the inset table.

As observed in the 30-week study, the curves demonstrate that patients assigned to either placebo or to donepezil hydrochloride have a wide range of responses, but that the donepezil hydrochloride treated patients are more likely to show greater improvements in cognitive performance.

Effects on the CIBIC-plus: Figure 6 is a histogram of the frequency distribution of CIBIC-plus scores attained by patients assigned to each of the three treatment groups who completed 12 weeks of treatment. The differences in mean scores for donepezil hydrochloride treated patients compared to the patients on placebo at Week 12 were 0.36 and 0.38 points for the 5 mg/day and 10 mg/day treatment groups, respectively. These differences were statistically significant.

In both studies, patient age, sex and race were not found to predict the clinical outcome of donepezil hydrochloride treatment.

14.2 Severe Alzheimer’s Disease

The effectiveness of donepezil hydrochloride in the treatment of patients with severe Alzheimer’s Disease was established in studies employing doses of 10 mg/day.

Swedish 6 Month Study

The effectiveness of donepezil hydrochloride as a treatment for severe Alzheimer’s disease is demonstrated by the results of a randomized, double-blind, placebo-controlled clinical study conducted in Sweden (6 month study) in patients with probable or possible Alzheimer’s disease diagnosed by NINCDS-ADRDA and DSM-IV criteria, MMSE: range of 1 to 10. Two hundred and forty eight (248) patients with severe Alzheimer’s disease were randomized to donepezil hydrochloride or placebo. For patients randomized to donepezil hydrochloride, treatment was initiated at 5 mg once daily for 28 days and then increased to 10 mg once daily. At the end of the 6 month treatment period, 90.5% of the donepezil hydrochloride treated patients were receiving the 10 mg/day dose. The mean age of patients was 84.9 years, with a range of 59 to 99. Approximately 77 % of patients were women, and 23 % were men. Almost all patients were Caucasian. Probable AD was diagnosed in the majority of the patients (83.6% of donepezil hydrochloride treated patients and 84.2% of placebo treated patients).

Study Outcome Measures: The effectiveness of treatment with donepezil hydrochloride was determined using a dual outcome assessment strategy that evaluated cognitive function using an instrument designed for more impaired patients and overall function through caregiver-rated assessment. This study showed that patients on donepezil hydrochloride experienced significant improvement on both measures compared to placebo.

The ability of donepezil hydrochloride to improve cognitive performance was assessed with the Severe Impairment Battery (SIB). The SIB, a multi-item instrument, has been validated for the evaluation of cognitive function in patients with moderate to severe dementia. The SIB evaluates selective aspects of cognitive performance, including elements of memory, language, orientation, attention, praxis, visuospatial ability, construction, and social interaction. The SIB scoring range is from 0 to 100, with lower scores indicating greater cognitive impairment.

Daily function was assessed using the Modified Alzheimer’s Disease Cooperative Study Activities of Daily Living Inventory for Severe Alzheimer’s Disease (ADCS-ADL-severe).The ADCS-ADL-severe is derived from the Alzheimer’s Disease Cooperative Study Activities of Daily Living Inventory, which is a comprehensive battery of ADL questions used to measure the functional capabilities of patients. Each ADL item is rated from the highest level of independent performance to complete loss. The ADCS-ADL-severe is a subset of 19 items, including ratings of the patient’s ability to eat, dress, bathe, use the telephone, get around (or travel), and perform other activities of daily living; it has been validated for the assessment of patients with moderate to severe dementia. The ADCS-ADL-severe has a scoring range of 0 to 54, with the lower scores indicating greater functional impairment. The investigator performs the inventory by interviewing a caregiver, in this study a nurse staff member, familiar with the functioning of the patient.

Effects on the SIB:

Figure 7 shows the time course for the change from baseline in SIB score for the two treatment groups over the 6 months of the study. At 6 months of treatment, the mean difference in the SIB change scores for donepezil hydrochloride treated patients compared to patients on placebo was 5.9 points. Donepezil hydrochloride treatment was statistically significantly superior to placebo.

Figure 8 illustrates the cumulative percentages of patients from each of the two treatment groups who attained the measure of improvement in SIB score shown on the X-axis. While patients assigned both to donepezil hydrochloride and to placebo have a wide range of responses, the curves show that the donepezil hydrochloride group is more likely to show a greater improvement in cognitive performance.

Effects on the ADCS-ADL-severe: Figure 9 illustrates the time course for the change from baseline in ADCS-ADL-severe scores for patients in the two treatment groups over the 6 months of the study. After 6 months of treatment, the mean difference in the ADCS-ADL-severe change scores for donepezil hydrochloride treated patients compared to patients on placebo was 1.8 points. Donepezil hydrochloride treatment was statistically significantly superior to placebo.

Figure 10 shows the cumulative percentages of patients from each treatment group with specified changes from baseline ADCS-ADL-severe scores. While both patients assigned to donepezil hydrochloride and placebo have a wide range of responses, the curves demonstrate that the donepezil hydrochloride group is more likely to show a smaller decline or an improvement.

Japanese 24-Week Study

In a study of 24 weeks duration conducted in Japan, 325 patients with severe Alzheimer’s disease were randomized to doses of 5 mg/day or 10 mg/day of donepezil, administered once daily, or placebo. Patients randomized to treatment with donepezil were to achieve their assigned doses by titration, beginning at 3 mg/day, and extending over a maximum of 6 weeks. Two hundred and forty eight (248) patients completed the study, with similar proportions of patients completing the study in each treatment group. The primary efficacy measures for this study were the SIB and CIBIC-plus.

At 24 weeks of treatment, statistically significant treatment differences were observed between the 10 mg/day dose of donepezil and placebo on both the SIB and CIBIC-plus. The 5 mg/day dose of donepezil showed a statistically significant superiority to placebo on the SIB, but not on the CIBIC-plus.

16 HOW SUPPLIED/STORAGE AND HANDLING

16.1. Donepezil Hydrochloride Tablets

Supplied as film-coated, round tablets containing either 5 mg or 10 mg of donepezil HCl.

The 5 mg tablets are white. The strength, in mg (5), is debossed on one side and a stylized G is debossed on the other side.

Blisters of 30 (NDC# 67046-128-30)

The 10 mg tablets are yellow. The strength, in mg (10), is debossed on one side and a stylized G is debossed on the other side.

Blisters of 30 (NDC# 67046-129-30)

Storage: Store at 20° - 25° C (68° - 77° F) [See USP Controlled Room Temperature].

17 PATIENT COUNSELING INFORMATION

See FDA-approved Patient Package Insert attached to this label.

To assure safe and effective use of donepezil hydrochloride tablets, the information and instructions provided in the attached Patient Package Insert should be discussed with patients and caregivers.

Patients and caregivers should be instructed to take donepezil hydrochloride tablets only once per day, as prescribed.

Patients and caregivers should be instructed that donepezil hydrochloride tablets should not be split or crushed. Donepezil hydrochloride tablets should be swallowed whole.

Patients and caregivers should be advised that the product may cause nausea, diarrhea, insomnia, vomiting, muscle cramps, fatigue and decreased appetite.

PATIENT PACKAGE INSERT

DONEPEZIL HYDROCHLORIDETABLETS

Rx only

Read the Patient Information that comes with donepezil hydrochloride tablets before the patient starts taking it and each time you get a refill. There may be new information. This leaflet does not take the place of talking with the doctor about Alzheimer’s disease or treatment for it. If you have questions, ask the doctor or pharmacist.

What are donepezil hydrochloride tablets?

Donepezil hydrochloride comes as donepezil hydrochloride film-coated tablets in dosage strengths of 5 mg and 10 mg.

Donepezil hydrochloride tablets are a prescription medicine to treat mild, moderate, and severe Alzheimer’s disease (up to 10 mg). Donepezil hydrochloride tablets can help with mental function and with doing daily tasks. Donepezil hydrochloride does not work the same in all people. Some people may:

- Seem much better
- Get better in small ways or stay the same
- Get worse over time but slower than expected
- Not change and then get worse as expected

Donepezil hydrochloride tablets do not cure Alzheimer’s disease. All patients with Alzheimer’s disease get worse over time, even if they take donepezil hydrochloride tablets.

Donepezil hydrochloride tablets have not been approved as a treatment for any medical condition in children.

Who should not take donepezil hydrochloride tablets?

The patient should not take donepezil hydrochloride tablets if allergic to any of the ingredients in donepezil hydrochloride tablets or to medicines that contain piperidines. Ask the patient’s doctor if you are not sure. See the end of this leaflet for a list of ingredients in donepezil hydrochloride tablets.

What should I tell the doctor before the patient takes donepezil hydrochloride tablets?

Tell the doctor about all the patient’s present or past health problems.

Include:

- Any heart problems including problems with irregular, slow, or fast heartbeats
- Asthma or lung problems
- A seizure
- Stomach ulcers
- Difficulty passing urine
- Liver or kidney problems
- Trouble swallowing tablets
- Present pregnancy or plans to become pregnant. It is not known if donepezil hydrochloride tablets can harm an unborn baby.
- Present breast-feeding. It is not known if donepezil hydrochloride passes into breast milk. Donepezil hydrochloride tablets are not for women who are breast-feeding.

Tell the doctor about all the medicines the patient takes, including prescription and non-prescription medicines, vitamins, and herbal products. Donepezil hydrochloride tablets and other medicines may affect each other.

Be particularly sure to tell the doctor if the patient takes aspirin or medicines called nonsteroidal anti-inflammatory drugs (NSAIDs). There are many NSAID medicines, both prescription and non-prescription. Ask the doctor or pharmacist if you are not sure if any of the patient’s medicines are NSAIDs. Taking NSAIDs and donepezil hydrochloride tablets together may make the patient more likely to get stomach ulcers.

Donepezil hydrochloride tablets taken with certain medicines used for anesthesia may cause side effects. Tell the responsible doctor or dentist that the patient takes donepezil hydrochloride tablets before the patient has:

- surgery
- medical procedures
- dental surgery or procedures

Know the medicines that the patient takes. Keep a list of all the patient’s medicines. Show it to the doctor or pharmacist before the patient starts a new medicine.

How should the patient take donepezil hydrochloride tablets?

- Give donepezil hydrochloride tablets exactly as prescribed by the doctor. Do not stop donepezil hydrochloride tablets or change the dose yourself. Talk with the doctor first.
- Give donepezil hydrochloride tablets one time each day. Donepezil hydrochloride tablets can be taken with or without food.
- Donepezil hydrochloride tablets should be swallowed whole without the tablets being broken or crushed.
- If you miss giving the patient a dose of donepezil hydrochloride tablets, just wait. Give only the next dose at the usual time. Do not give 2 doses at the same time.
- If donepezil hydrochloride tablets are missed for 7 days or more, talk with the doctor before starting again.
- If the patient takes too much donepezil hydrochloride tablets at one time, call the doctor or poison control center, or go to the emergency room right away.

What are the possible side effects of donepezil hydrochloride tablets?

Donepezil hydrochloride tablets may cause the following serious side effects:

- slow heartbeat and fainting. This happens more often in people with heart problems. Call the doctor right away if the patient faints while taking donepezil hydrochloride tablets.
- more stomach acid. This raises the chance of ulcers and bleeding. The risk is higher for patients who had ulcers, or take aspirin or other NSAIDs.
- worsening of lung problems in people with asthma or other lung disease.
- seizures.
- difficulty passing urine.

Call the doctor right away if the patient has:

- fainting.
- heartburn or stomach pain that is new or won’t go away.
- nausea or vomiting, blood in the vomit, dark vomit that looks like coffee grounds.
- bowel movements or stools that look like black tar.
- new or worse asthma or breathing problems.
- seizures.
- difficulty passing urine.

The most common side effects of donepezil hydrochloride tablets are:

- nausea
- diarrhea
- not sleeping well
- vomiting
- muscle cramps
- feeling tired
- not wanting to eat

These side effects may get better after the patient takes donepezil hydrochloride tablets for a while. This is not a complete list of side effects with donepezil hydrochloride tablets. For more information, ask the doctor or pharmacist.

Call your doctor for medical advice about side effects. You may report side effects to FDA at 1-800-FDA-1088.

How should donepezil hydrochloride tablets be stored?

Store donepezil hydrochloride tablets at room temperature between 68 ○ - 77° F (20○ - 25○ C).

Keep donepezil hydrochloride tablets and all medicines out of the reach of children.

General information about donepezil hydrochloride tablets

Medicines are sometimes prescribed for conditions that are not mentioned in this Patient Information Leaflet. Do not use donepezil hydrochloride tablets for a condition for which it was not prescribed. Do not give donepezil hydrochloride tablets to people other than the patient, even if they have the same symptoms as the patient, as it may harm them.

This leaflet summarizes the most important information about donepezil hydrochloride tablets. If you would like more information talk with the patient’s doctor. You can ask your pharmacist or doctor for information about donepezil hydrochloride tablets that is written for health professionals.

What are the ingredients in donepezil hydrochloride tablets?

Active ingredient: donepezil hydrochloride

Inactive ingredients:

Donepezil HCl 5 mg and 10 mg film-coated tablets: lactose monohydrate, cornstarch, microcrystalline cellulose, hydroxypropyl cellulose, and magnesium stearate. The film coating contains talc, polyethylene glycol, hypromellose, and titanium dioxide. Additionally, the 10 mg tablet contains yellow iron oxide (synthetic) as a coloring agent.

Manufactured by Eisai Inc., Woodcliff Lake, NJ 07677
Distributed by Greenstone LLC, Peapack, NJ 07977

Repackaged by:
Contract Pharmacy Services-PA
125 Titus Ave Suite 200
Warrington, PA 18976 USA

Original--1/2011--NJW

Rx Only

© 2010

PRINCIPAL DISPLAY PANEL

5 mg Tablets

PRINCIPAL DISPLAY PANEL

10 mg Tablets